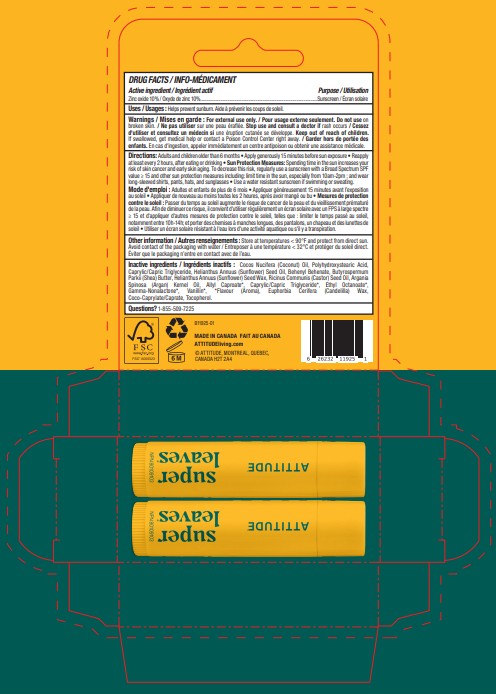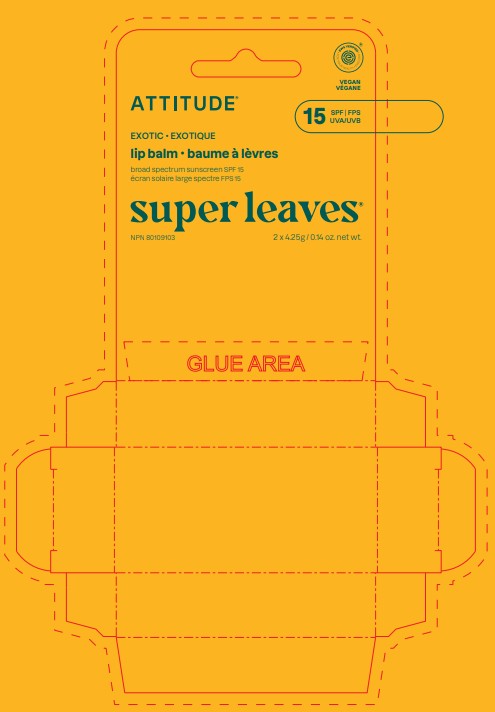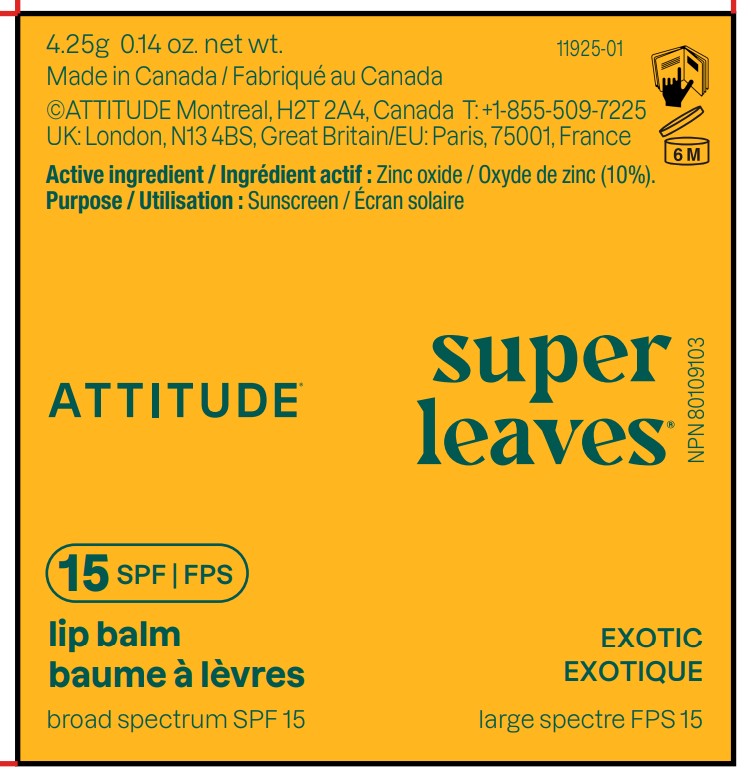 DRUG LABEL: ATTITUDE Super leaves Lip Balm SPF 15 Exotic
NDC: 61649-925 | Form: STICK
Manufacturer: 9055-7588 Québec Inc.DBA ATTITUDE
Category: otc | Type: HUMAN OTC DRUG LABEL
Date: 20251203

ACTIVE INGREDIENTS: ZINC OXIDE 10 g/100 g
INACTIVE INGREDIENTS: ALLYL CAPROATE; ETHYL OCTANOATE; CAPRYLIC/CAPRIC TRIGLYCERIDE; VANILLIN; RICINUS COMMUNIS (CASTOR) SEED OIL; EUPHORBIA CERIFERA (CANDELILLA) WAX; ARGANIA SPINOSA KERNEL OIL; BEHENYL BEHENATE; COCO-CAPRYLATE/CAPRATE; HELIANTHUS ANNUUS (SUNFLOWER) SEED WAX; HELIANTHUS ANNUUS (SUNFLOWER) SEED OIL; BUTYROSPERMUM PARKII (SHEA) BUTTER; COCOS NUCIFERA (COCONUT) OIL; TOCOPHEROL; POLYHYDROXYSTEARIC ACID (2300 MW); .GAMMA.-NONALACTONE

ATTITUDE Super leaves Lip Balm SPF 15 Exotic

DRUG FACTS

ACTIVE INGREDIENT

Zinc oxide (10 %)

PURPOSE

Sunscreen

INDICATIONS AND USAGE

Helps prevent sunburn

WARNINGS

For external use only.

Do not use on broken skin.

Keep out of reach of children. If swallowed, get medical help or contact a Poison Control Center right away.

Stop use and consult a doctor if rash occurs.

DOSAGE AND ADMINISTRATION

Adults and children older than 6 months • Apply generously 15 minutes before sun exposure • Reapply at least every 2 hours, after eating or drinking • Sun Protection Measures: Spending time in the sun increases your risk of skin cancer and early skin aging. To decrease this risk, regularly use a sunscreen with a Broad Spectrum SPF value ≥ 15 and other sun protection measures including: limit time in the sun, especially from 10am-2pm ; and wear long-sleeved shirts, pants, hats, and sunglasses • Use a water resistant sunscreen if swimming or sweating.

INACTIVE INGREDIENT

Cocos Nucifera (Coconut) Oil, Polyhydroxystearic Acid, Caprylic/Capric Triglyceride, Helianthus Annuus (Sunflower) Seed Oil, Behenyl Behenate, Butyrospermum Parkii (Shea) Butter, Helianthus Annuus (Sunflower) Seed Wax, Ricinus Communis (Castor) Seed Oil, Argania Spinosa (Argan) Kernel Oil, Allyl Caproate*, Caprylic/Capric Triglyceride*, Ethyl Octanoate*, Euphorbia Cerifera (Candelilla) Wax, Gamma-Nonalactone*, Vanillin*, *Flavour (Aroma), Coco-Caprylate/Caprate, Tocopherol.

STORAGE AND HANDLING

Store at temperatures < 90°F and protect from direct sun. Avoid contact of the packaging with water

Questions ? 1-855-509-7225

PACKAGE LABEL

ATTITUDE

EWG Verified

VEGAN

SPF 15

UVA ¦ UVB

exotic

lip balm

Broad spectrum sunscreen SPF 15

super leaves

2 x 4.25 g / 0.14 oz. net wt.

NPN 80109103

Made in Canada